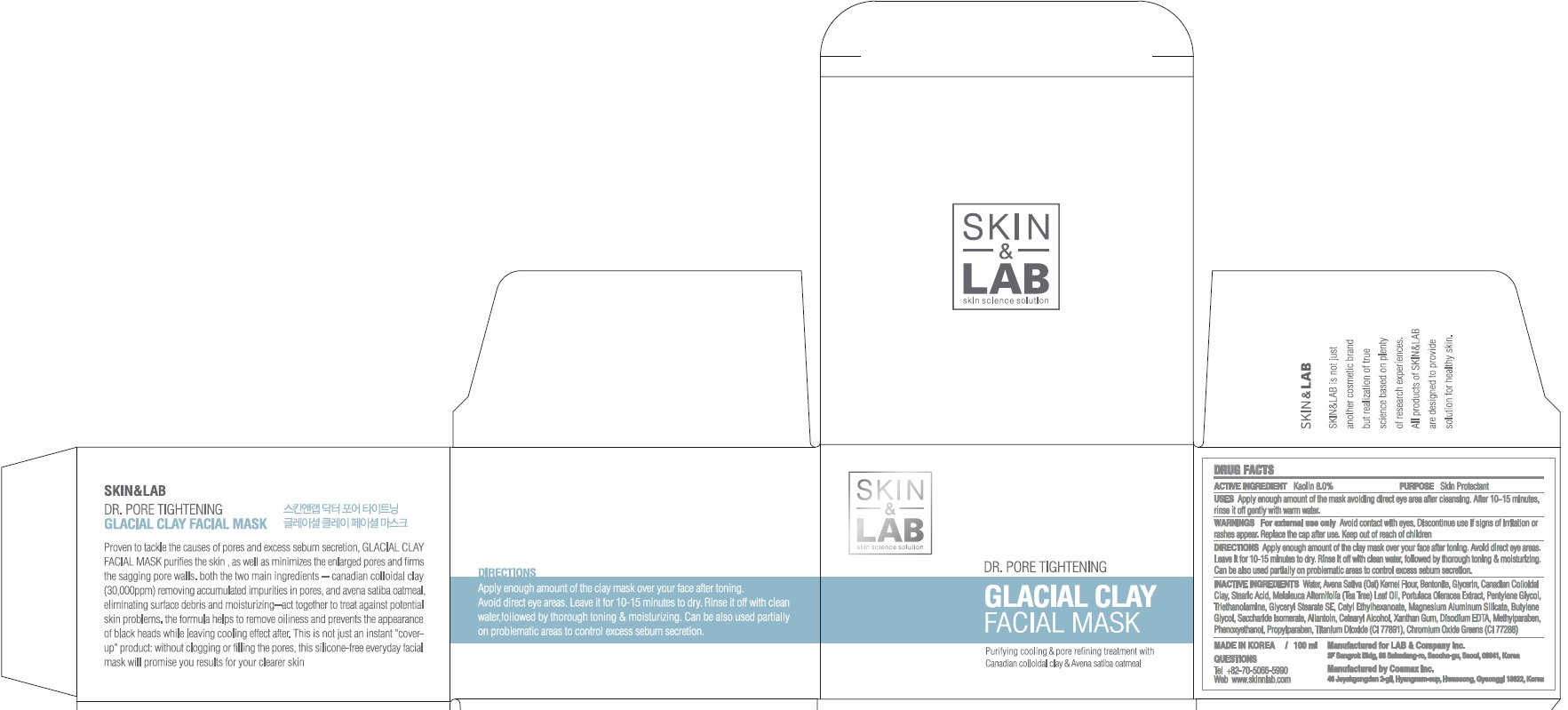 DRUG LABEL: Dr Pore Tightening GLACIAL CLAY FACIAL MASK
NDC: 69457-050 | Form: CREAM
Manufacturer: LAB & Company Inc.
Category: otc | Type: HUMAN OTC DRUG LABEL
Date: 20171207

ACTIVE INGREDIENTS: Kaolin 8.0 g/100 mL
INACTIVE INGREDIENTS: Water; Glycerin

ACTIVE INGREDIENT

Active ingredients: Kaolin 8.0%

INACTIVE INGREDIENT

Inactive ingredients: Water, Avena Sativa (Oat) Kernel Flour, Bentonite, Glycerin, Canadian Colloidal Clay, Stearic Acid, Melaleuca Alternifolia (Tea Tree) Leaf Oil, Portulaca Oleracea Extract, Pentylene Glycol, Triethanolamine, Glyceryl Stearate SE, Cetyl Ethylhexanoate, Magnesium Aluminum Silicate, Butylene Glycol, Saccharide Isomerate, Allantoin, Cetearyl Alcohol, Xanthan Gum, Disodium EDTA, Methylparaben, Phenoxyethanol, Propylparaben, Titanium Dioxide (CI 77891), Chromium Oxide Greens (CI 77288)

PURPOSE

Purpose: Skin Protectant

WARNINGS

Warnings: For external use only. Avoid contact with eyes. Discontinue use if signs of irritation or rashes appear. Replace the cap after use. Keep out of reach of children.

Keep out of reach of children: Keep out of reach of babies and children.

QUESTIONS

Tel: +82-70-5066-5990

Web: www.skinnlab.com

Uses

Uses: Apply enough amount of the mask avoiding direct eye area after cleasning. After 10~15 minutes, rinse it off gently with warm water.

Directions

Directions: Apply enough amount of the clay mask over your face after toning. Avoid direct eye areas. Leave it for 10-15 minutes to dry. Rinse it off with clean water, followed by thorough toning & moisturizing. Can be also used partially on problematic areas to control excess sebum secretion.